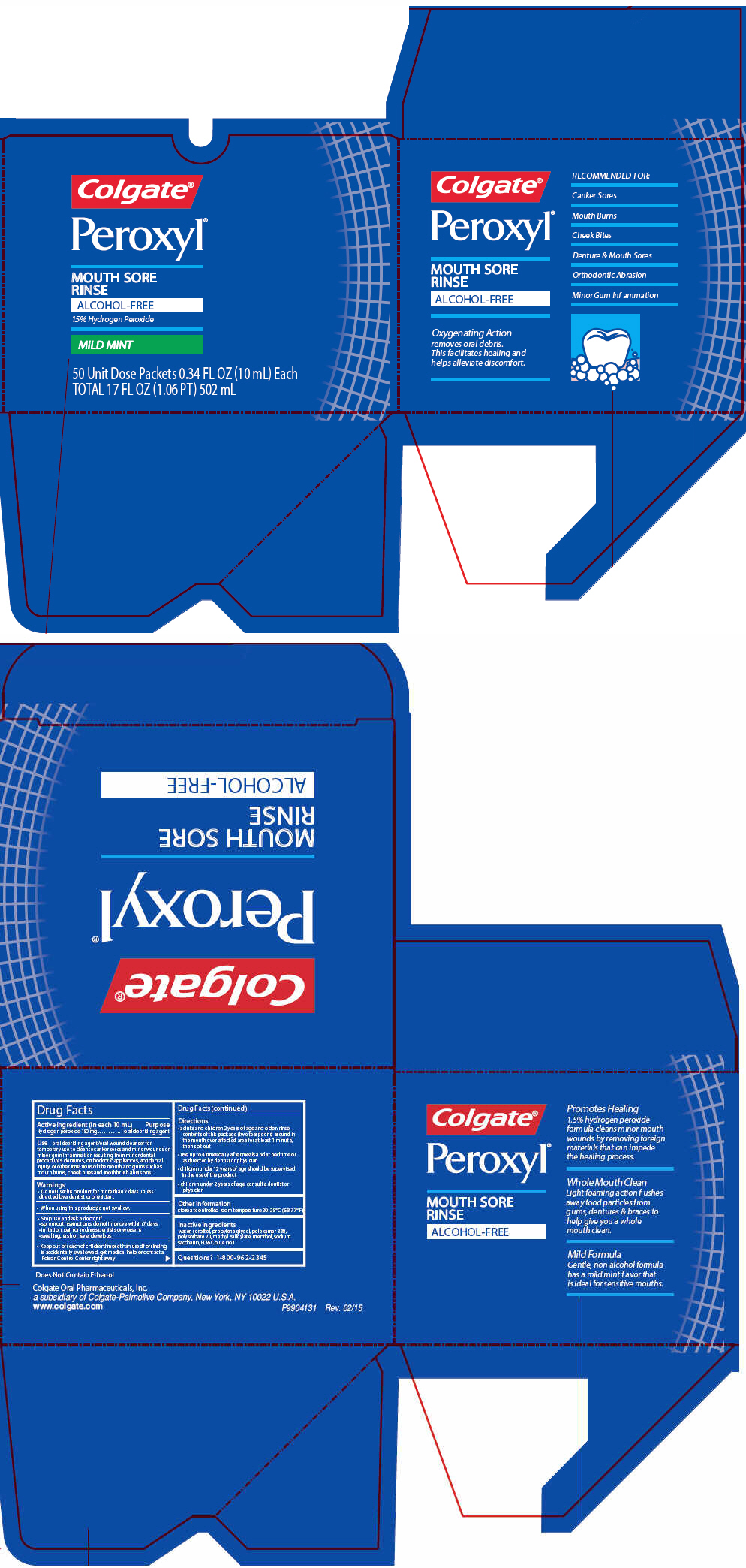 DRUG LABEL: PEROXYL MOUTH SORE MILD MINT
NDC: 0126-0083 | Form: RINSE
Manufacturer: Colgate Oral Pharmaceuticals, Inc.
Category: otc | Type: HUMAN OTC DRUG LABEL
Date: 20150908

ACTIVE INGREDIENTS: Hydrogen Peroxide 15 mg/1 mL
INACTIVE INGREDIENTS: Water; Sorbitol; Propylene Glycol; Poloxamer 338; FD&C BLUE NO. 1; Polysorbate 20; Saccharin Sodium

PEROXYL® MOUTH SORE RINSE MILD MINT

Drug Facts

Active ingredient (in each 10 mL)

Hydrogen peroxide 150 mg

Purpose

oral debriding agent

Use

oral debriding agent/oral wound cleanser for temporary use to cleanse canker sores and minor wounds or minor gum inf ammation resulting from minor dental procedures, dentures, orthodontic appliances, accidental injury, or other irritations of the mouth and gums such as mouth burns, cheek bites and toothbrush abrasions.

Warnings

- Do not use this product for more than 7 days unless directed by a dentist or physician.

- When using this product, do not swallow.

- Stop use and ask a doctor if
  - sore mouth symptoms do not improve within 7 days
  - irritation, pain or redness persists or worsens
  - swelling, rash or fever develops

- Keep out of reach of children. If more than used for rinsing is accidentally swallowed, get medical help or contact a Poison Control Center right away.

Directions

- adults and children 2 years of age and older: rinse contents of this package (two teaspoons) around in the mouth over affected area for at least 1 minute, then spit out
- use up to 4 times daily after meals and at bedtime or as directed by dentist or physician
- children under 12 years of age should be supervised in the use of the product
- children under 2 years of age: consult a dentist or physician

Other information

store at controlled room temperature 20-25° C (68-77° F)

Inactive ingredients

water, sorbitol, propylene glycol, poloxamer 338, polysorbate 20, methyl salicylate, menthol, sodium saccharin, FD&C blue no.1

Questions?

1-800-962-2345

PRINCIPAL DISPLAY PANEL - 50 Packet Carton

Colgate®

Peroxyl®

MOUTH SORE
RINSE
ALCOHOL-FREE
1.5% Hydrogen Peroxide

MILD MINT

50 Unit Dose Packets 0.34 FL OZ (10 mL) Each
TOTAL 17 FL OZ (1.06 PT) 502 mL